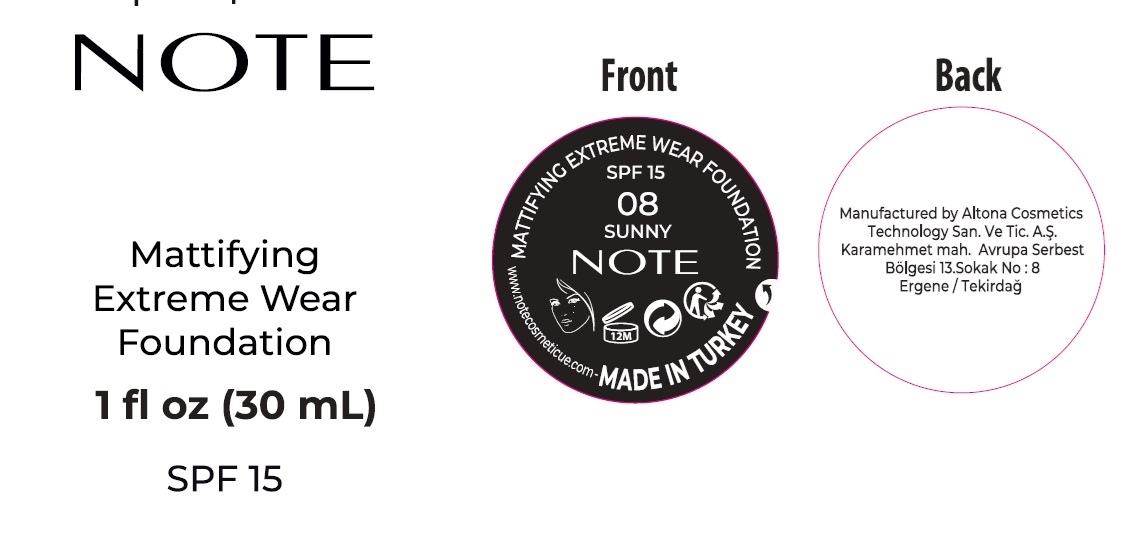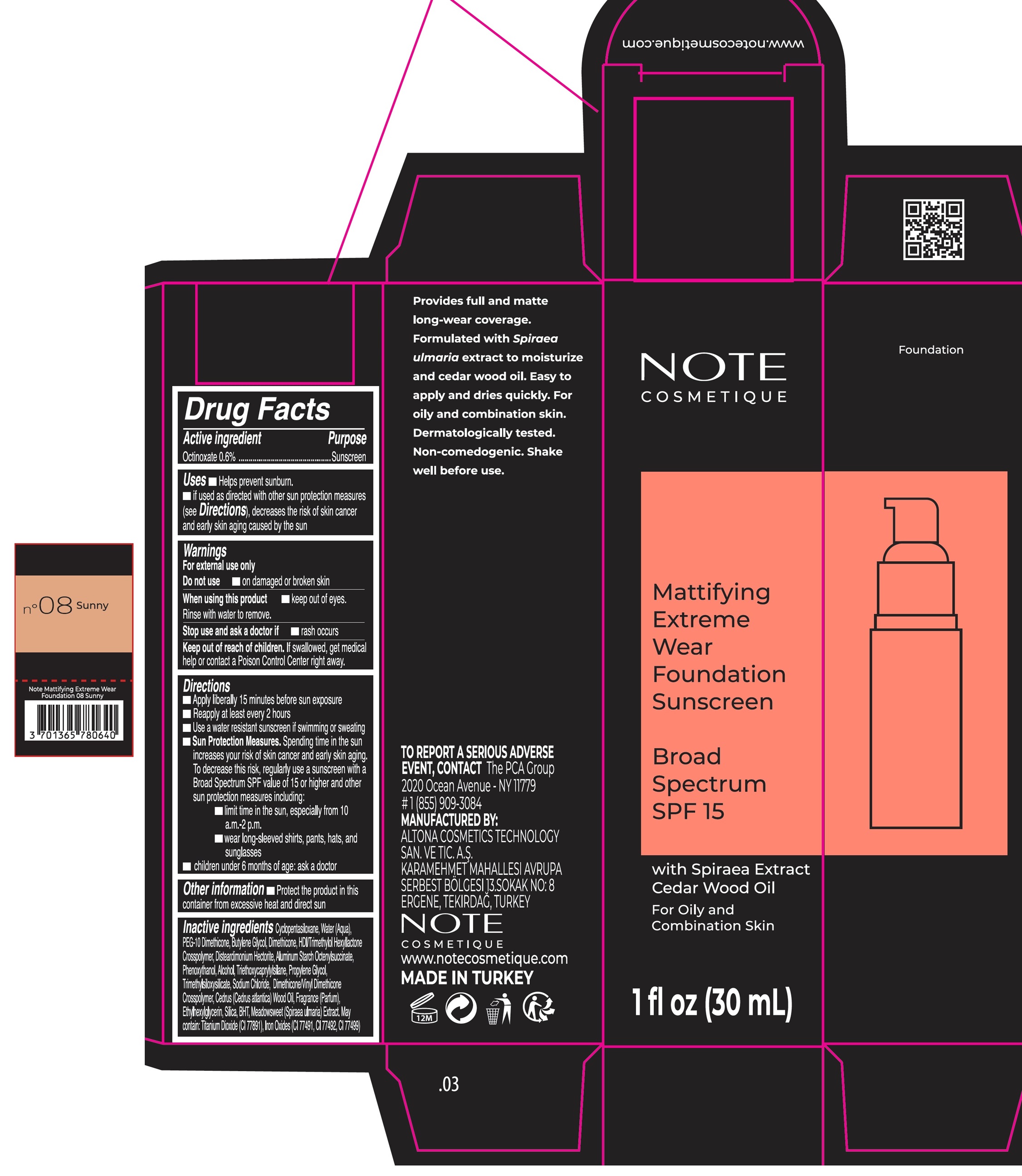 DRUG LABEL: Note Mattifying Extreme Wear Foundation 08 Sunny
NDC: 70474-005 | Form: CREAM
Manufacturer: ALTONA COSMETICS TECHNOLOGY SANAYI VE TICARET ANONIM SIRKETI
Category: otc | Type: HUMAN OTC DRUG LABEL
Date: 20240916

ACTIVE INGREDIENTS: OCTINOXATE 6 mg/1 mL
INACTIVE INGREDIENTS: CYCLOMETHICONE 5; WATER; BUTYLENE GLYCOL; DIMETHICONE, UNSPECIFIED; HEXAMETHYLENE DIISOCYANATE/TRIMETHYLOL HEXYLLACTONE CROSSPOLYMER; DISTEARDIMONIUM HECTORITE; ALUMINUM STARCH OCTENYLSUCCINATE; PHENOXYETHANOL; ALCOHOL; TRIETHOXYCAPRYLYLSILANE; PROPYLENE GLYCOL; SODIUM CHLORIDE; ETHYLHEXYLGLYCERIN; SILICON DIOXIDE; BUTYLATED HYDROXYTOLUENE; FILIPENDULA ULMARIA ROOT; CEDRUS ATLANTICA WOOD OIL

Note Mattifying Extreme Wear Foundation SPF 15, 08 Sunny

Active ingredient

Octinoxate 0.6%

Purpose

Sunscreen

Uses

- Helps prevent sunburn.
- if used as directed with other sun protection measures (see Directions), decreases the risk of skin cancer and early skin aging caused by the sun

Warnings

For external use only

Do not use

- on damaged or broken skin

When using this product

- keep out of eyes. Rinse with water to remove.

Stop use and ask a doctor if

- rash occurs

Keep out of reach of children.

If swallowed, get medical help or contact a Poison Control Center right away.

Directions

- Apply liberally 15 minutes before sun exposure
- Reapply at least every 2 hours
- Use a water resistant sunscreen if swimming or sweating
- Sun Protection Measures. Spending time in the sun increases your risk of skin cancer and early skin aging. To decrease this risk, regularly use a sunscreen with a Broad Spectrum SPF value of 15 or higher and other sun protection measures including:
- limit time in the sun, especially from 10 a.m.-2 p.m.
- wear long-sleeved shirts, pants, hats, and sunglasses
- children under 6 months of age: ask a doctor

Other information

- Protect the product in this container from excessive heat and direct sun

Inactive ingredients

Cyclopentasiloxane, Water (Aqua), PEG-10 Dimethicone, Butylene Glycol, Dimethicone, HDI/Trimethylol Hexyllactone Crosspolymer, Disteardimonium Hectorite, Aluminum Starch Octenylsuccinate, Phenoxyethanol, Alcohol, Triethoxycaprylylsilane, Propylene Glycol, Trimethylsiloxysilicate, Sodium Chloride, Dimethicone/Vinyl Dimethicone Crosspolymer, Cedrus (Cedrus atlantica) Wood Oil, Fragrance (Parfum), Ethylhexylglycerin, Silica, BHT, Meadowsweet (Spiraea ulmaria) Extract, May contain: Titanium Dioxide (CI 77891), Iron Oxides (CI 77491, CI 77492, CI 77499)